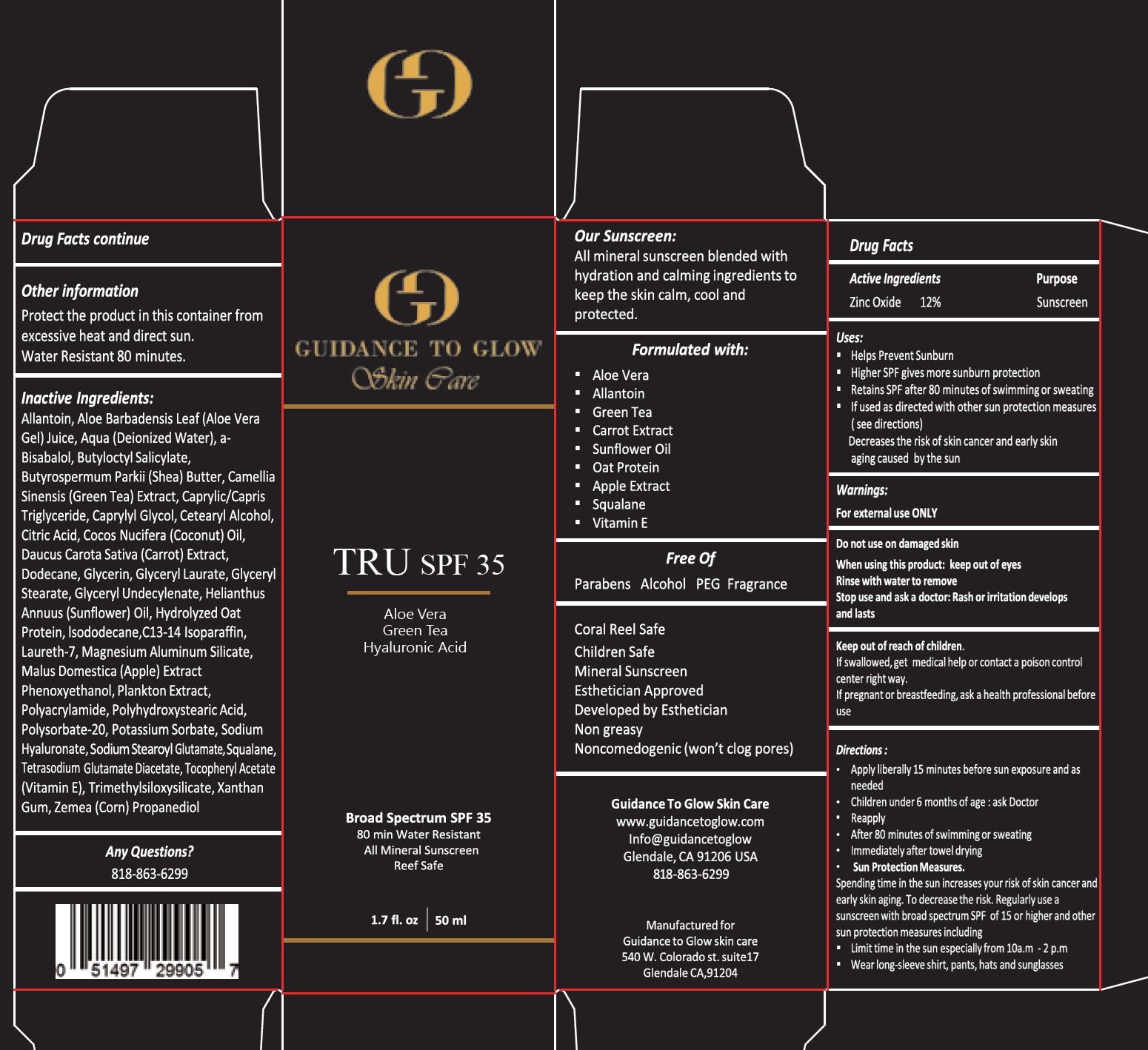 DRUG LABEL: GUIDANCE TO GLOW TRU SPF 35
NDC: 84444-506 | Form: CREAM
Manufacturer: GUIDANCE TO GLOW SKIN CARE
Category: otc | Type: HUMAN OTC DRUG LABEL
Date: 20240625

ACTIVE INGREDIENTS: ZINC OXIDE 120 mg/1 mL
INACTIVE INGREDIENTS: ALLANTOIN; ALOE VERA LEAF; WATER; BUTYLOCTYL SALICYLATE; SHEA BUTTER; GREEN TEA LEAF; MEDIUM-CHAIN TRIGLYCERIDES; CAPRYLYL GLYCOL; CETOSTEARYL ALCOHOL; CITRIC ACID MONOHYDRATE; COCONUT OIL; CARROT; DODECANE; GLYCERIN; GLYCERYL LAURATE; HELIANTHUS ANNUUS FLOWERING TOP; ISODODECANE; C13-14 ISOPARAFFIN; LAURETH-7; MAGNESIUM ALUMINUM SILICATE; APPLE; POLYSORBATE 20; POTASSIUM SORBATE; HYALURONATE SODIUM; SODIUM STEAROYL GLUTAMATE; SQUALANE; TETRASODIUM GLUTAMATE DIACETATE; .ALPHA.-TOCOPHEROL ACETATE; XANTHAN GUM; CORN

GUIDANCE TO GLOW TRU SPF-35

Active Ingredients

Zinc Oxide 12%

Purpose

Sunscreen

Uses:

- Helps Prevent Sunburn
- Higher SPF gives more sunburn protection
- Retains SPF after 80 minutes of swimming or sweating
- If used as directed with other sun protection measures (see directions)

Decreases the risk ok skin cancer and early skin aging caused by the sun

Warnings:

For external use ONLY

Do not use

on damaged skin

When using this product:

keep out of eyes Rinse with water to remove

Stop use and ask a doctor:

Rash or irritation develops and lasts

Keep out of reach of children.

If swallowed,get medical help or contact a poison control center right way.

If pregnant or breastfeeding,

ask a health professional before use

Directions:

- Apply liberally 15 minutes before sun exposure and as needed
- Children under 6 months of age: ask a doctor
- Reapply
- After 80 minutes of swimming or sweating
- Immediately after towel drying
- Sun Protection Measures.

Spending time in the sun increases your risk of skin cancer and early skin aging. To decrease this risk. Regularly use sunscreen with broad spectrum SPF of 15 or higher and other sun protection measures including

- Limit time in the sun especially from 10a.m - 2 p.m
- Wear long-sleeve shirts, pants, hats, and sunglasses

Other information

Protect the product in this container from excessive heat and direct sun.

Water Resistant 80 minutes.

Inactive Ingredients:

Allantoin, Aloe Barbadensis Leaf (Aloe Vera Gel) Juice, Aqua (Deionized Water), a-Bisabalol, Butyloctyl Salicylate, Butyrospermum Parkii (Shea) Butter, Camellia Sinensis (Green Tea) Extract, Caprylic/Capris Triglyceride, Caprylyl Glycol, Cetearyl Alcohol, Citric Acid, Cocos Nucifera (Coconut) Oil, Daucus Carota Sativa (Carrot) Extract, Dodecane, Glycerin, Glyceryl Laurate, Glyceryl Stearate, Glyceryl Undecylenate, Helianthus Annuus (Sunflower) Oil, Hydrolyzed Oat Protein, Isododecane, C13-14 Isoparaffin, Laureth-7, Magnesium Aluminum Silicate, Malus Domestica (Apple) Extract Phenoxyethanol, Plankton Extract, Polyacrylamide, Polyhydroxystearic Acid, Polysorbate-20, Potassium Sorbate, Sodium Hyaluronate, Sodium Stearoyl Glutamate, Squalane, Tetrasodium Glutamate Diacetate, Tocopheryl Acetate (Vitamin E), Trimethylsiloxysilicate, Xanthan Gum, Zemea (Corn) Propanediol

Any Questions?

818-863-6299